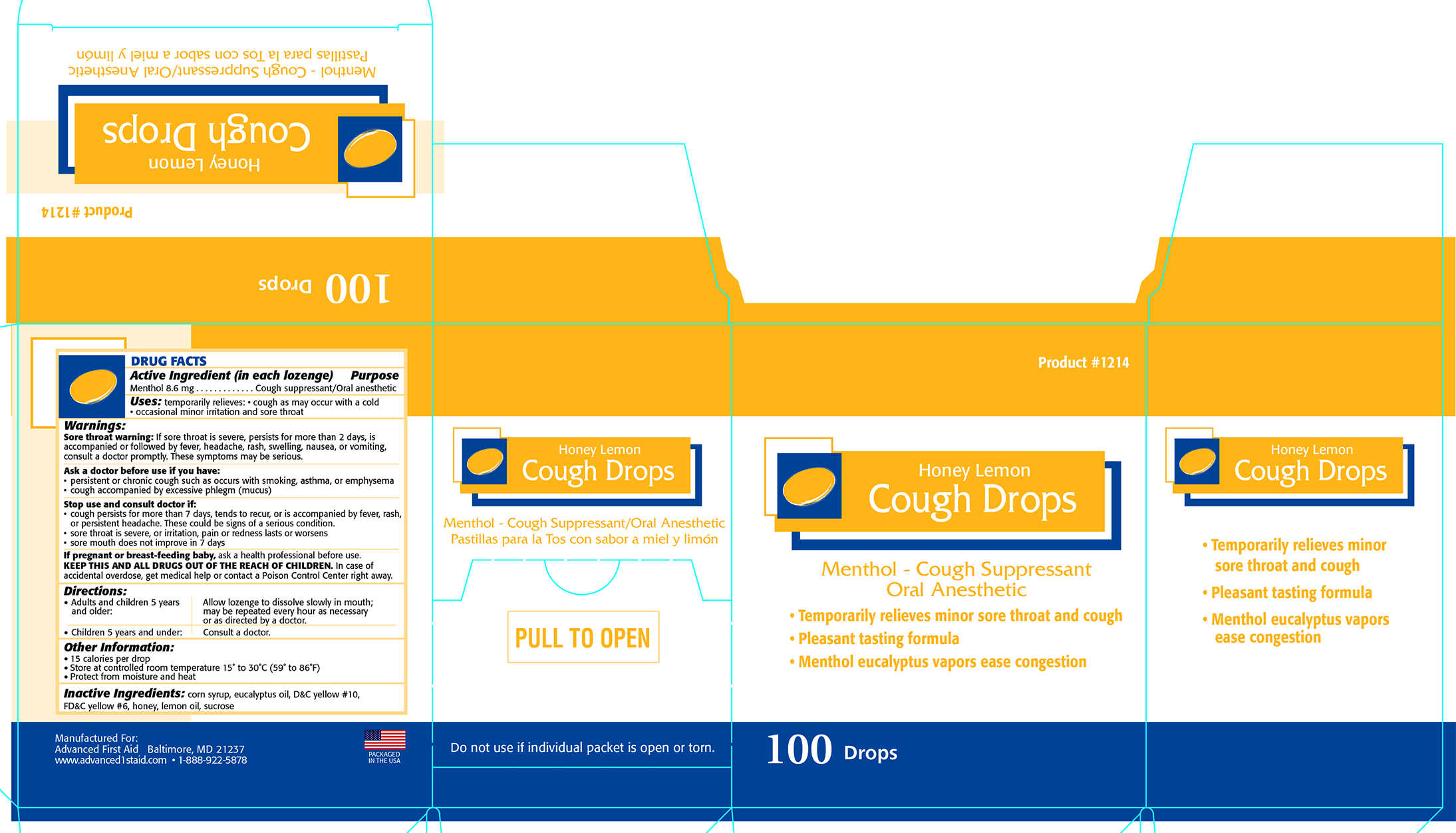 DRUG LABEL: ADVANCED HONEY LEMON COUGH DROPS
NDC: 67060-121 | Form: LOZENGE
Manufacturer: ADVANCED FIRST AID, INC.
Category: otc | Type: HUMAN OTC DRUG LABEL
Date: 20190807

ACTIVE INGREDIENTS: MENTHOL 8.6 1/1 1
INACTIVE INGREDIENTS: SUCROSE; CORN SYRUP; EUCALYPTUS OIL; D&C YELLOW NO. 10; FD&C YELLOW NO. 6; HONEY; LEMON OIL

Active Ingredient (in each lozenge) - Menthol 8.6mg

PURPOSE

Cough suppressant / Oral Anesthetic

INDICATIONS AND USAGE

Uses: temporarily relieves • cough as may occur with a cold • occasional minor irritation and sore throat

Warnings:

Sore throat warning: If sore throat is severe, persists for more than 2 days, is accompanied or followed by fever, headache, rash, swelling, nausea, or vomiting, consult a doctor promptly. These smptoms may be serious.

Ask a doctor before use if you have: • persistent or chronic cough such as ocurs with smoking, asthma, or emphysema

• cough accompanied by excessive phlegm (mucus)

Stop use and consult a doctor if:

• cough persists for more than 7 days, tends to recur, or is accompanied by fever, rash or persistent headache. These could be signs of a serious condition.

• sore throat is severe, or irritation, pain or redness lasts or worsens

• sore mouth does not improve in 7 days

PREGNANCY OR BREAST FEEDING

If pregnant or breast-feeding baby, ask a health professional before use.

KEEP OUT OF REACH OF CHILDREN

KEEP THIS AND ALL DRUGS OUT OF REACH OF CHILDREN. In case of accidental overdose, get medical help or contact a Poison Control Center right away.

Directions:

• Adults and children 5 years and older: Allow lozenge to dissolve slowly in mouth; may be repeated every hour as necessary or as directed by a doctor.

• Children under 5 years: Consult a doctor.

INACTIVE INGREDIENT

corn syrup, eucalyptus oil, D&C Yellow #10, FD& C Yellow #6, honey, lemon oil, sucrose